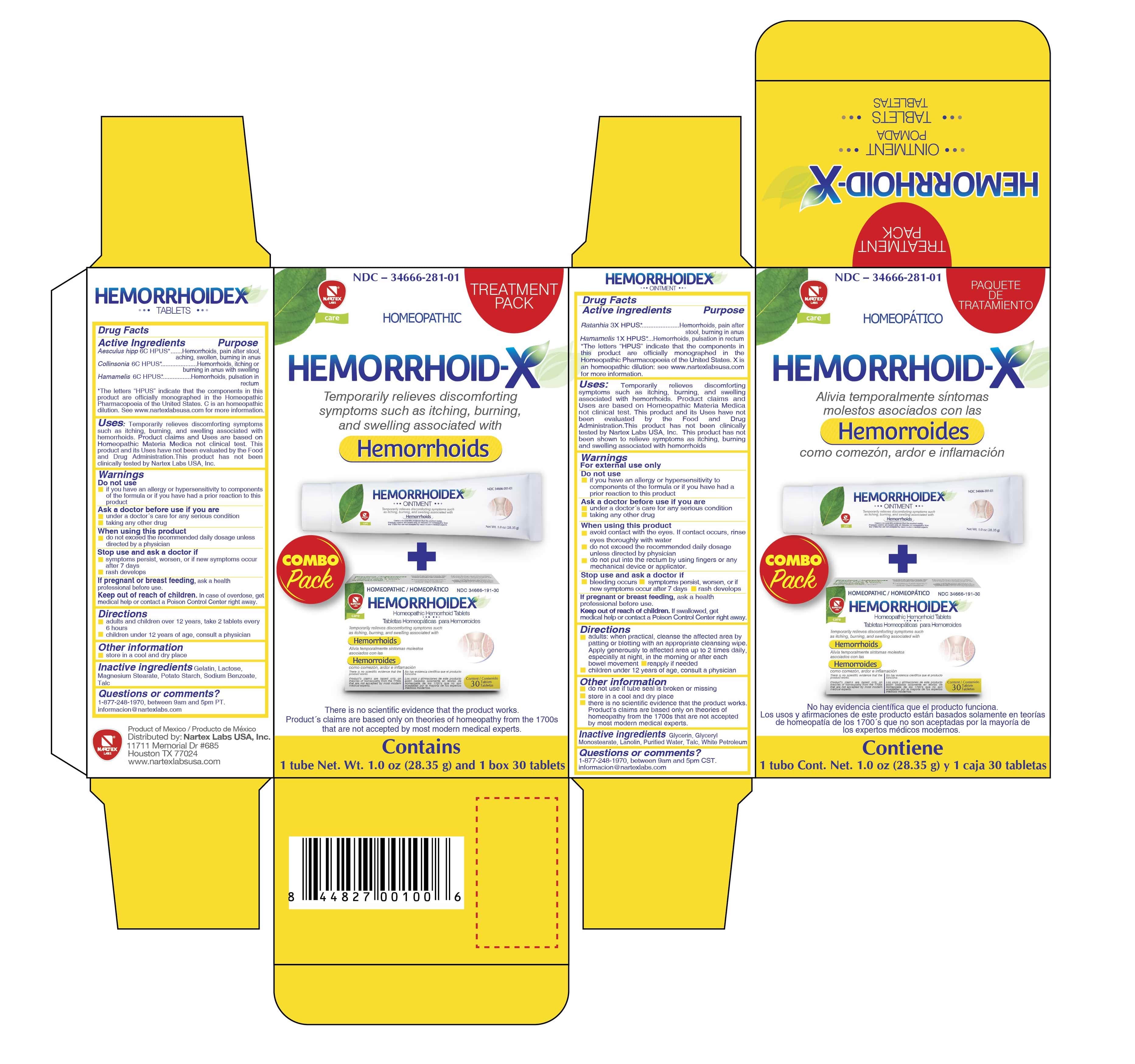 DRUG LABEL: Hemorrhoid-X Treatment Pack
NDC: 34666-291 | Form: KIT | Route: ORAL
Manufacturer: Nartex Laboratorios Homeopaticos SA DE CV
Category: homeopathic | Type: HUMAN OTC DRUG LABEL
Date: 20190412

ACTIVE INGREDIENTS: COLLINSONIA CANADENSIS WHOLE 6 [hp_C]/1 1; AESCULUS HIPPOCASTANUM WHOLE 6 [hp_C]/1 1; HAMAMELIS VIRGINIANA WHOLE 6 [hp_C]/1 1; KRAMERIA LAPPACEA WHOLE 3 [hp_X]/1 g; HAMAMELIS VIRGINIANA LEAF 1 [hp_X]/1 g
INACTIVE INGREDIENTS: SODIUM BENZOATE; LACTOSE, UNSPECIFIED FORM; STARCH, POTATO; TALC; GELATIN; MAGNESIUM STEARATE; WATER; PETROLATUM; GLYCERIN; TALC; GLYCERYL MONOSTEARATE; LANOLIN

Hemorrhoid-X Twin Pack

Active Ingredient (in each tablet)

Aesculus Hipp 6C HPUS*

Collinsonia 6C HPUS*

Hamamelis 6C HPUS*

Purpose

Aesculus Hipp 6C HPUS*.........Hemorrhoids, pain after stool, aching, swollen, burning in anus

Collinsonia 6C HPUS*.........Hemorrhoids, itching or burning in anus with swelling

Hamamelis 6C HPUS*.......Hemorrhoids, pulsation in rectum

*The letters "HPUS" indicate that the components in this product are officially monographed in the Homeopathic Pharmacopoeia of the United States. "C" is an homeopathic dilution. See www.nartexlabsusa.com formore information.

Uses

Temporarily relieves discomforting symptoms such as itching, burning, and swelling associated with hemorrhoids. Product claims and Uses are based on Homeopathic Materia Medica not clinical test. This product and its Uses have not been evaluated by the Food and Drug Administration. This product has not been clinically tested by Nartex Labs USA, Inc.

Ask a doctor before use if you are

- under a doctor's care for any serious condition
- taking any other drug

Stop use and ask a doctor if

- Symptoms persist, worsen, or if new symptoms occur after 7 days
- rash develops

When using this product

- do not exceed recommended daily dosage unless directed by a physcian.

PREGNANCY OR BREAST FEEDING

If pregnant or breastfeeding, ask a health professional before use.

Keep out of reach of children. If swallowed, get medical help or contact a Poison Control Center right away.

Directions

- Adults and childrenover 12 years: take 2 tablets every 6 hours
- Children under 12 years of age: consult a physician

Other Information

Store in a cool and dry place.

Inactive Ingredients

Gelatin, Lactose, Magnesium stearate, Potato stach, Sodium Benzoate, Talc

Questions or Comments?

Call 1-877-248-1970 between 9am and 5pm PT.

Informacion@nartexlabs.com

Product of Mexico / Producto de Mexico

Distributed by: Nartex Labs, USA, Inc.

11711 Memorial Drive #685

Houston, TX 77024

www.nartexlabsusa.com

Active Ingredients

Ratanhia 3X HPUS*

Hamamelis 1X HPUS*

Purpose

Ratanhia 3X HPUS*....Hemorrhoids, pain after stool, burning in anus

Hamamelis 1X HPUS*.......Hemorrhoids, pulsation in rectum

*The letters HPUS indicate that the components in this product are offically monographed in the Homeopathic Pharmacopoeia of the United States. X is an homeopathic dilution: see www.nartexlabsusa.com for more information.

Uses

Temporarily relieves discomforting symptoms such as itching, burning, and swelling associated with hemorrhoids. Product claims and Uses are based on Homeopathic Materia Medica not clinical test. This product and its Uses have not been evaluated by the Food and Drug Administration. This product has not been clinically tested by Nartex Labs USA, Inc. This product has not been shown to relieve symptoms such as itching, burning, and swelling associated with hemorrhoids.

Warnings

For external use only.

Do not use

- if you have an allergy or hypersensitivity to the components of the fourmal or have had a prior reaction to this product.

Ask a doctor before use if you are

under a doctor's care for any serious condition
taking any other drug

When using this product

- avoid contact with eyes. If contact occurs, rinse eyes thoroughly with water
- do not exceed the recommended daily dosage unless directed by physician
- do not put into the rectum by use of fingers or any mechanical device or applicator

Stop use and ask a doctor if

- bleeding occurs
- symptoms persist, worsen, or if new symtoms occur after 7 days
- rash develops

PREGNANCY OR BREAST FEEDING

If pregnant or breast feeding, consult a health professional before use,

Keep out of reach of children. If swallowed, get medical help or contact a Poison Control Center right away.

Directions

- Adults: when practical, cleanse the affected area by patting or blotting with an appropriate cleansing wipe. Apply generously to affected area up to 2 times daily, especially at night, in the morning or after each bowel movement.
- reapply if needed
- Children under 12 years of age, consult a phsyician.

Other Information

- do not use if tube seal is broken or missing
- store in a cool and dry place
- there is no scientific evidence that the product works. Product claims are based only on theories of homeopathy from the 1700's that are not accepted by most modern medical experts.

Inactive Ingredients

Glycerin, Glyceryl monostearate, Lanolin, Purifed water, Talc, White petrolatum

Questions or Comments?

1-877-248-1970 between 9am and 5pm CST.

informacion@nartexlabs.com

Principal Display Panel

TREATMENT PACK

HOMEOPATHIC

HEMORRHOID-X

Temporarily relieves discomforting symptoms such as itching, burning, and swelling associated with

Hemorroids

COMBO pack

There is no scientific evidence that the product works. Product's claims are based only on theories of homeopathy from the 1700's that are not accepted by most modern medical experts.

Contains

1 tube Net. Wt. 1.0oz (28.35g) and 1 box 30 tablets.